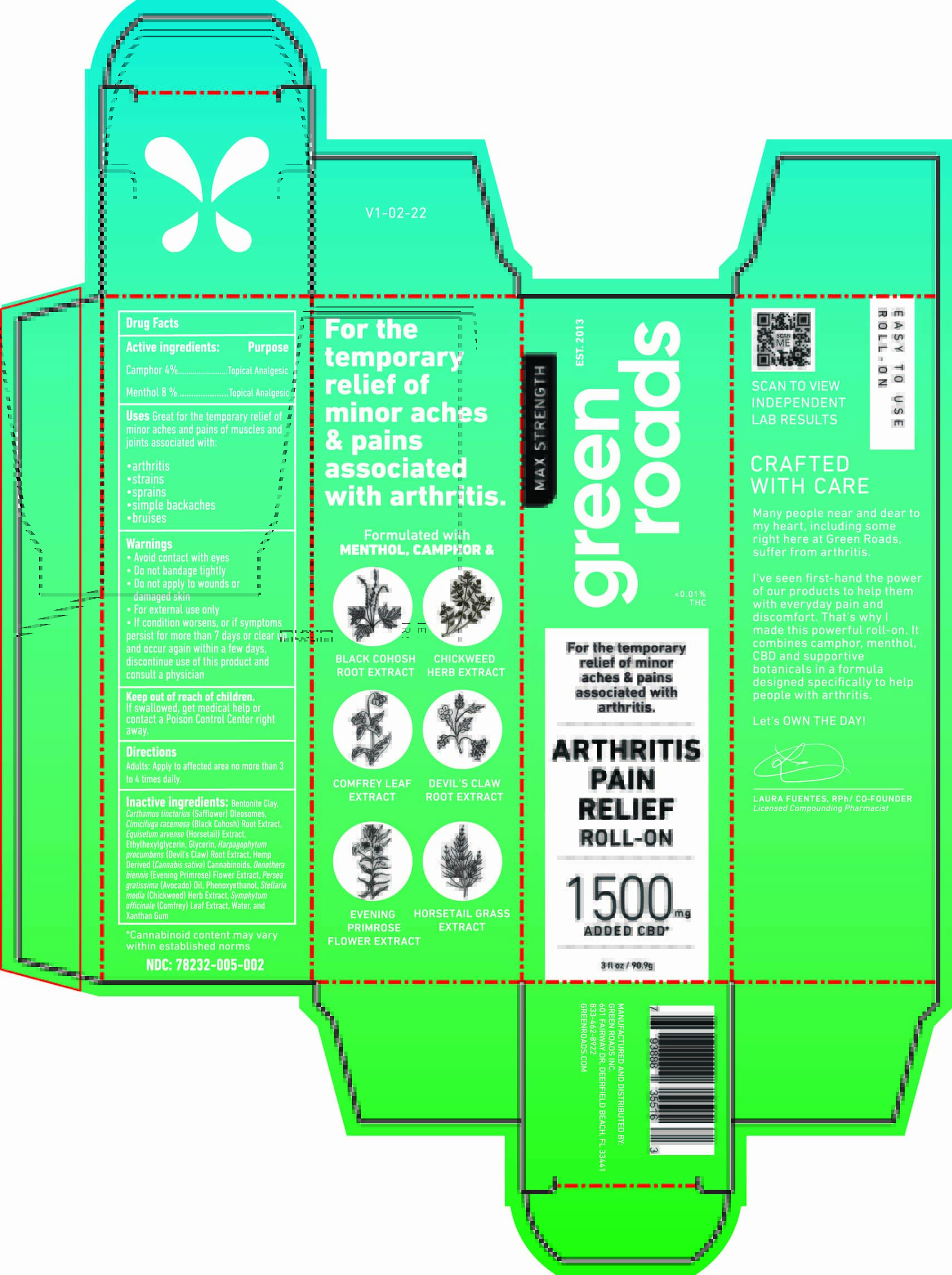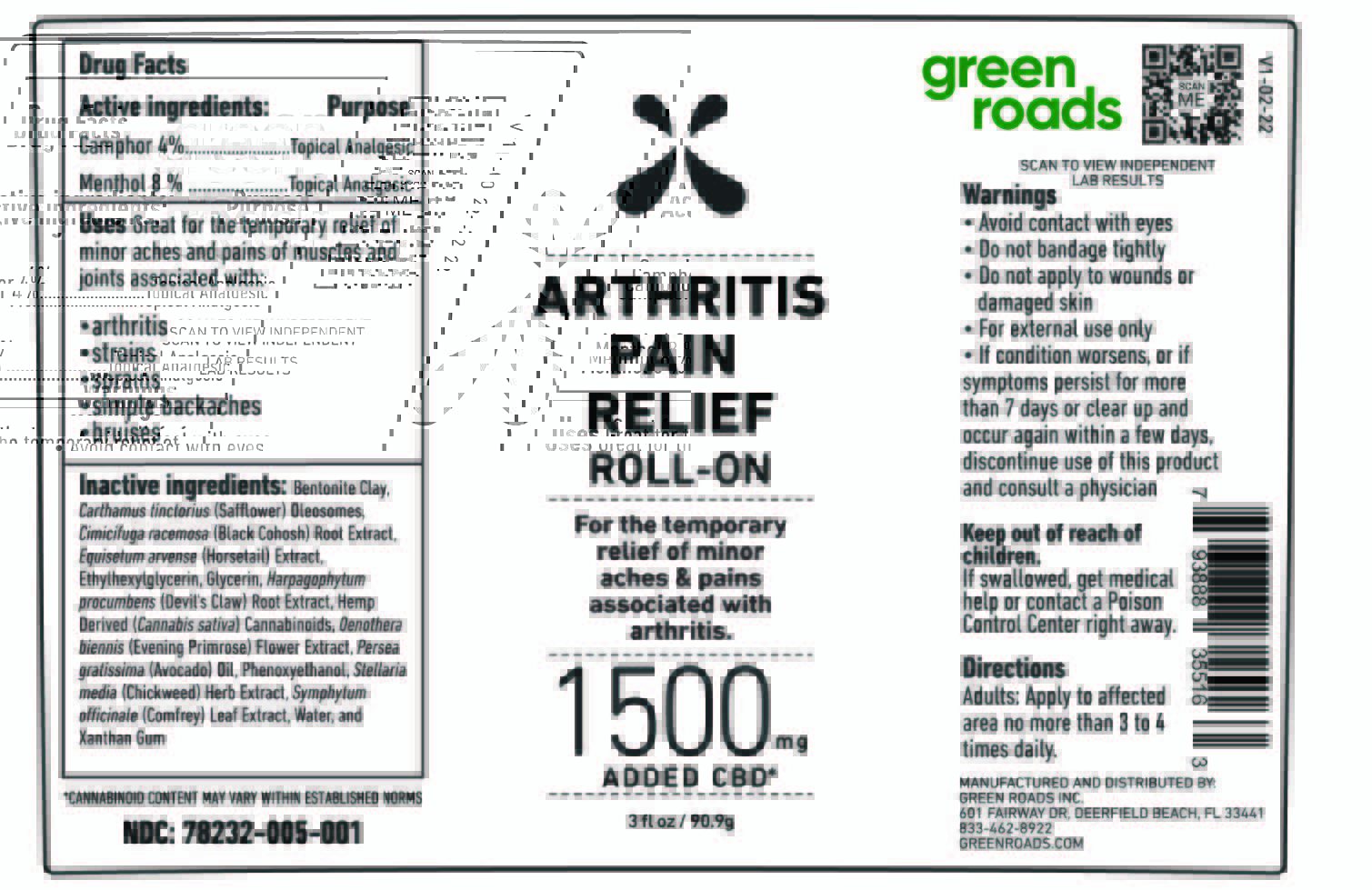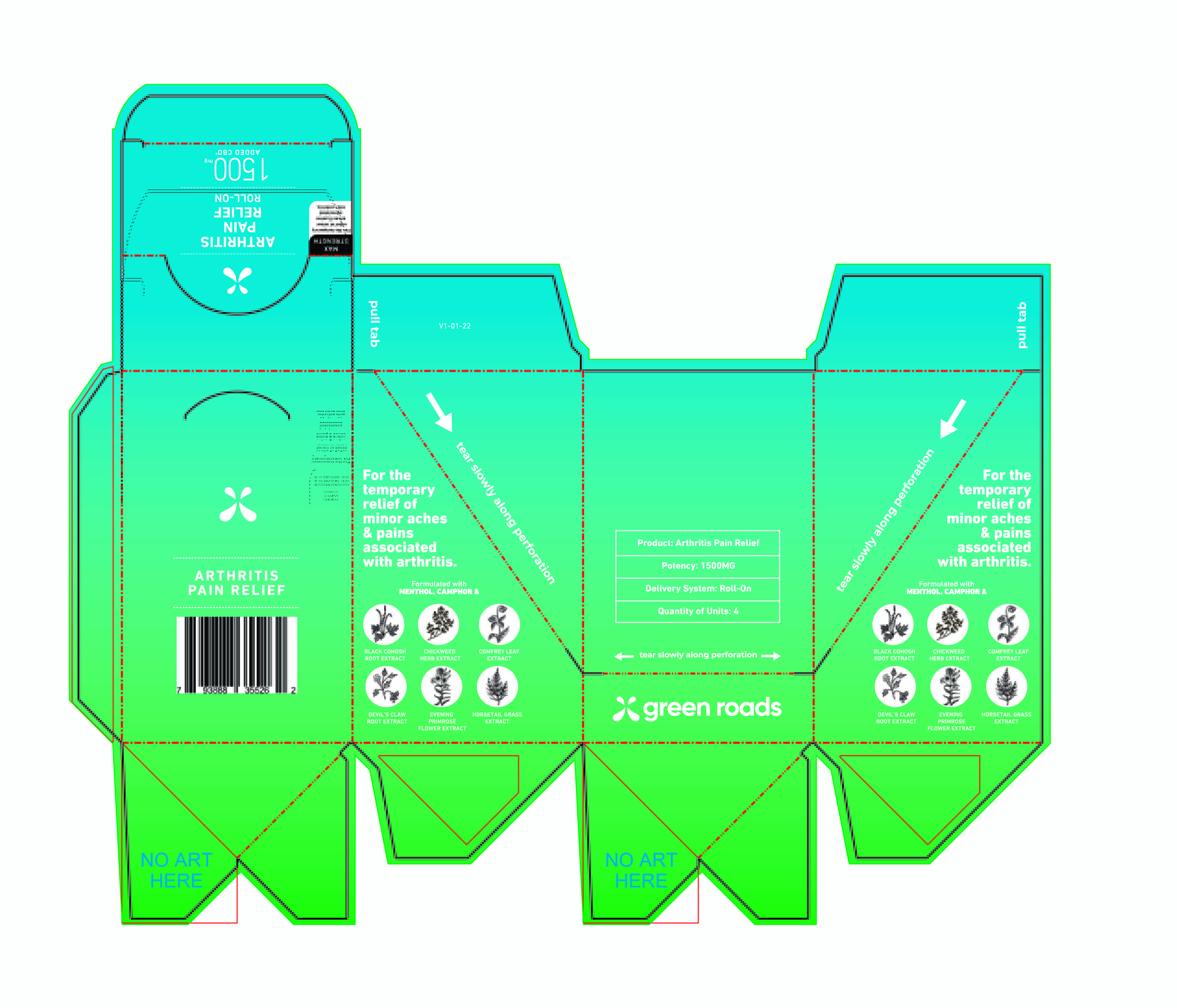 DRUG LABEL: GR Arthritis pain relief roll-on 1500 mg
NDC: 78232-005 | Form: LOTION
Manufacturer: Clarity Labs LLC
Category: otc | Type: HUMAN OTC DRUG LABEL
Date: 20220404

ACTIVE INGREDIENTS: MENTHOL 8 g/100 g; CAMPHOR (SYNTHETIC) 4 g/100 g
INACTIVE INGREDIENTS: OENOTHERA BIENNIS FLOWERING TOP 0.5 g/100 g; EQUISETUM ARVENSE WHOLE 0.5 g/100 g; HARPAGOPHYTUM PROCUMBENS ROOT 0.5 g/100 g; WATER 65 g/100 g; CARTHAMUS TINCTORIUS (SAFFLOWER) OLEOSOMES 12.5 g/100 g; BLACK COHOSH 0.5 g/100 g; ETHYLHEXYLGLYCERIN 0.1 g/100 g; PHENOXYETHANOL 0.9 g/100 g; AVOCADO OIL 2 g/100 g; CANNABIDIOL 2 g/100 g; SYMPHYTUM OFFICINALE WHOLE 0.5 g/100 g; BENTONITE 2.5 g/100 g; STELLARIA MEDIA 0.5 g/100 g

Arthritis pain relief roll-on 1500 mg 3 fl Oz / 90.9 g

This Arthritis Pain Relief lotion has been formulated with camphor and menthol to help with aches and pains, and then added cannabinoids, avocado oil, black cohosh, horsetail, and more to create a truly unique lotion for the wellbeing of muscles and joints.

Active Ingredients

Camphor 4% w/w. Purpose: Topical Analgesic

Menthol 8% w/w. Purpose: Topical Analgesic

Purpose

Topical Analgesic, pain relief lotion

Use

Pain relief lotion to help reduce minor aches and pains of muscles and joints associated with: arthritis, strains, sprains, simple backaches, and bruises.

Do not use

in children

on open skin wounds

WHEN USING

This product is for external use only.

When using this product keep out of eyes, ears, and mouth. In case of contact with eyes, rinse eyes thoroughly with water.

Do not bandage tightly when applying this product.

Do not apply this product more than 4 times per day.

Stop use and ask a doctor if irritation or rash occurs. If condition worsens, or if symptoms persist for more than 7 days or clear up and occur again within a few days, discontinue use of this product and consult a physician.

Keep out of reach of children. If swallowed, get medical help or contact a Poison Control Center right away.

Stop use and ask a doctor if irritation or rash occurs. If condition worsens, or if symptoms persist for more than 7 days or clear up and occur again within a few days, discontinue use of this product, and consult a physician.

Keep out of reach of children. If swallowed, get medical help, or contact a Poison Control Center right away.

Directions

This product is for external use only.

Rub the affected area accordingly.

Apply to affected area no more than 3 to 4 times daily.

Other information

Store between 15-30C (59-86F)

Avoid freezing and excessive heat above 40C (104F)

Inactive Ingredients

Bentonite Clay, Carthamus tinctorius (Safflower) Oleosomes, Cimicifuga racemose (Black Cohosh) Root Extract, Equisetum arvense (Horsetail) Extract, Ethylhexylglycerin, Glycerin, Harpagophylum procumbens (Devil's Claw) Root Extract, Hemp Derived (Cannabis sativa) Cannabinoids, Oenothera biennis (Evening Primrose) FlowerExtract, Persea gratissima (Avocado) Oil, Phenoxyethanol, Stellaria media (Chickweed) Herb Extract, Symphytum officinale (Comfrey) Leaf Extract, Water, and Xanthan Gum.

Manufacturing and Distributors information

MANUFACTURED AND DISTRIBUTED BY:

GREEN ROADS OF FLORIDA, LLC
601 FAIRWAY DR, DEERFIELD BEACH, FL 33441

833-462-8922
GREENROADS.COM

WARNINGS

Avoid contact with eyes

Do not bandage tightly

Do not apply to wounds or damaged skin

For external use only

Design and Label of CONTAINER

Tube Label

Package Label Display box (IFC)

IFC Individual Folding Carton

Most outer BOX

Big Container BOX